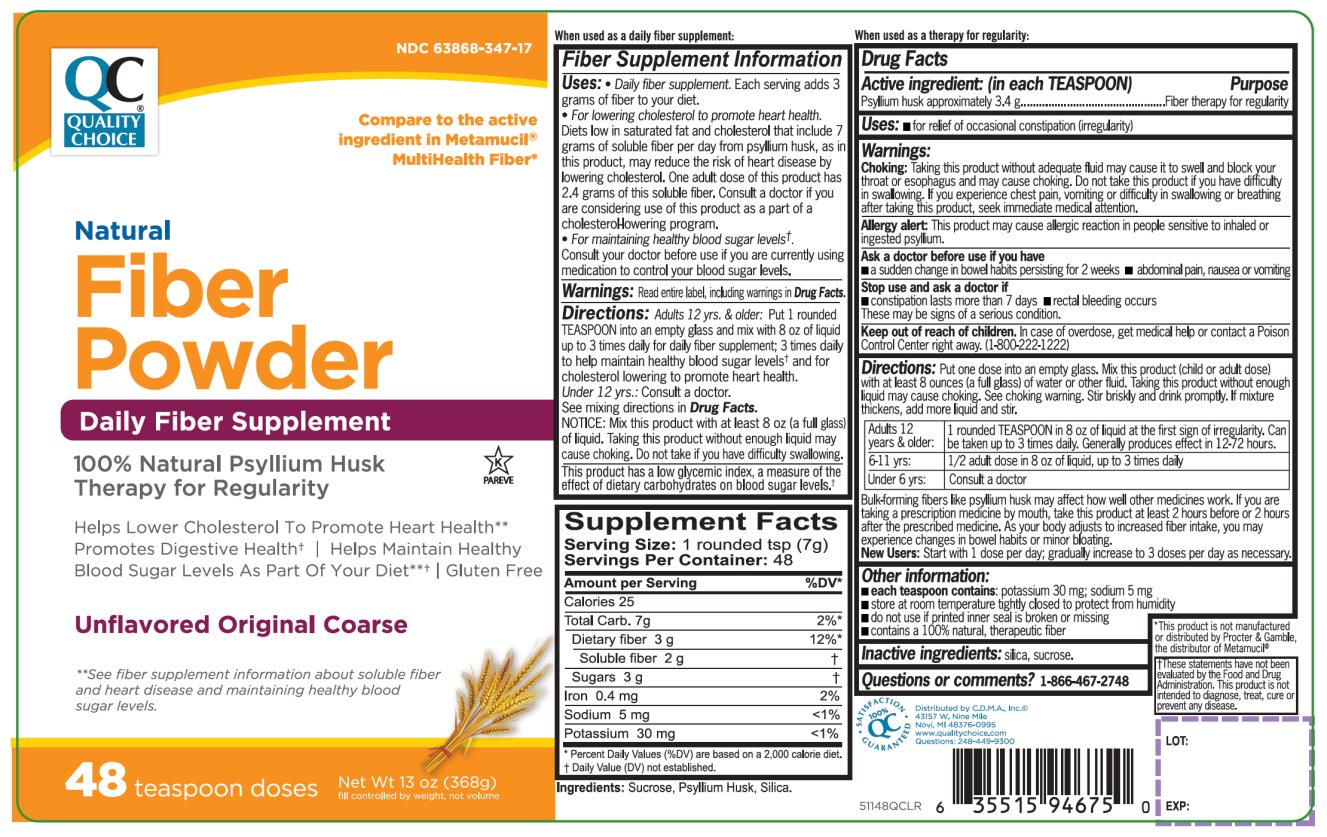 DRUG LABEL: Quality Choice
NDC: 63868-347 | Form: POWDER, FOR SUSPENSION
Manufacturer: QUALITY CHOICE (CHAIN DRUG MARKETING ASSOCIATION)
Category: otc | Type: HUMAN OTC DRUG LABEL
Date: 20210121

ACTIVE INGREDIENTS: PSYLLIUM HUSK 3.4 g/5.8 g
INACTIVE INGREDIENTS: SILICON DIOXIDE; SUCROSE

Quality Choice Natural Fiber Powder

Active ingredient (in each TEASPOON)

Psyllium husk approximately 3.4 g

Purpose

Fiber therapy for regularity

Uses

- for relief of occasional constipation (irregularity)

Warnings

Allergy alert: This product may cause allergic reaction in people sensitive to inhaled or ingested psyllium.

Choking: Taking this product without adequate fluid may cause it to swell and block your throat or esophagus and may cause choking. Do not take this product if you have difficulty in swallowing. If you experience chest pain, vomiting, or difficulty in swallowing or breathing after taking this product, seek immediate medical attention.

Ask a doctor before use if you have

- abdominal pain, nausea or vomiting
- a sudden change in bowel habits persisting for 2 weeks

Stop use and ask a doctor if

- Constipation lasts more than 7 days
- Rectal bleeding occurs

These may be signs of a serious condition.

Keep Out of Reach of Children

In case of overdose, get medical help or contact a Poison Control Center right away at 1-800-222-1222.

Directions:

Put one dose into an empty glass. Mix this product (child or adult dose) with at least 8 ounces (a full glass) of water or other fluid. Taking this product without enough liquid may cause choking. See choking warning. Stir briskly and drink promptly. If mixture thickness, add more liquid and stir.

Adults 12 years & older: | 1 rounded TEASPOON in 8 oz of liquid at the signs of irregularity. Can be taken up to 3 times daily. Generally produces effect in 12-72 hours.
6-11 yrs: | ½ adult dose in 8 oz of liquid, up to 3 times daily
Under 6 yrs: | Consult a doctor

Bulk-forming fibers like psyllium husk may affect how well other medicines work. If t=you are taking a prescription medicine by mouth, take this product at least 2 hours before or 2 hours after the prescribed medicine. As your body adjusts to increased fiber intake, you may experience changes in bowel habits or minor bloating.

New Users: Start with 1 dose per day; gradually increase to 3 doses per day as necessary

Other information

- each teaspoon contains: potassium 30 mg and sodium 5 mg
- Store at room temperature tightly closed to protect from humidity
- Do not use if printed inner seal is broken or missing
- Contains a 100% natural, therapeutic fiber

Inactive ingredients

silica, sucrose.

Questions or comments?

1-866-467-2748

Fiber Supplement Information

Uses:

- Daily fiber supplement. Each serving adds 3 grams of fiber to your diet.
- For lowering cholesterol to promote heart health. Diets low in saturated fat and cholesterol that include 7 grams of soluble fiber per day from psyllium husk, as in this product, may reduce the risk of heart disease by lowering cholesterol. One adults dose of this products has 2.4 grams of this soluble fiber. Consult a doctor if you are considering use of this product as a part of a cholesterol lowering program.

Warnings Read entire label, including warnings in Drug Facts.

Directions Adults 12 years and older: put 1 rounded TEASPOON in to an empty glass and mix with 8 oz of liquid up to 3 times daily for daily fiber supplement; 3 times daily to help maintain healthy blood sugar levels† and for cholesterol lowering to promote heart health.

under 12 years: Consult a doctor.

See mixing directions in Drug Facts.

NOTICE: Mix this product with at least 8 ounces (a full glass) of liquid. Taking this product without enough liquid may cause choking. Do not take if you have difficulty swallowing. See choking warning.

This product has a low glycemic index, a measure of the effect of dietary carbohydrates on blood sugar levels†.

Principal Display Panel

QUALITY CHOICE®

NDC# 63868-347-17

Compare to the active ingredient in Metamucil® MultiHealth Fiber*

Natural Fiber Powder

100% Natural Psyllium Husk

Daily Fiber Supplement | Therapy for Regularity

Helps Lower Cholesterol to Promote Heart Health**

Promotes Digestive Health†

Helps Maintain Healthy Blood Sugar Levels as Part of Your Diet**†

Gluten Free

Unflavored Original Coarse

**See fiber supplement information about soluble fiber and heart disease and maintaining healthy blood sugar levels.

48 teaspoon doses

K PAREVE

Net Wt. 13 oz (368g)

fill controlled by weight, not volume

100% QC SATISFACTION GUARANTEED

†These statements have not been evaluated by the Food and Drug Administration. This product is not intended to diagnose, treat, cure or prevent any disease.

*This product is not manufactured or distributed by Procter & Gamble, the distributor, the distributor of Metamucil®.

Distributed by C.D.M.A., Inc. ©

43157 W. Nine Mile

Novi, MI 48376-0995

www.qualitychoice.com

Questions: 248-449-9300